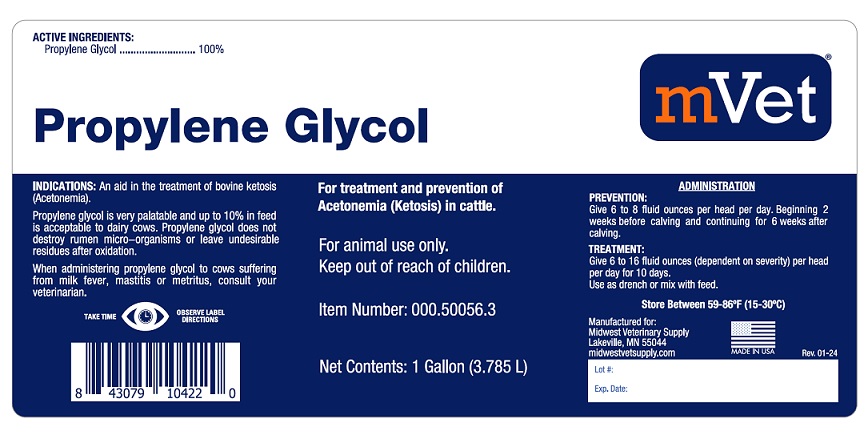 DRUG LABEL: PROPYLENE GLYCOL
NDC: 86223-055 | Form: LIQUID
Manufacturer: Midwest Veterinary Supply, Inc.
Category: animal | Type: OTC ANIMAL DRUG LABEL
Date: 20250508

ACTIVE INGREDIENTS: PROPYLENE GLYCOL 3.785 L/3.785 L

PROPYLENE GLYCOL

Propylene Glycol

ACTIVE INGREDIENTS:

Propylene Glycol ...................... 100%

For treatment and prevention of Acetonemia (Ketosis) in cattle.

For animal use only.

Keep out of reach of children.

INDICATIONS:

An aid in the treatment for bovine ketosis (Acetonemia).

Propylene glycol is very palatable and up to 10% in feed is acceptable to dairy cows. Propylene glycol does not destroy rumen micro-organisms or leave undesirable residues after oxidation.

When administering propylene glycol to cows suffering from milk fever, mastitis or metritus, consult your veterinarian.

ADMINISTRATION:

PREVENTION: Give 6 to 8 fluid ounces per head per day. Beginning 2 weeks before calving and continuing for 6 weeks after calving.

TREATMENT: Give 6 to 16 fluid ounces (dependent oN severity) per head per day for 10 days.

Use as drench or mix with feed.

Store Between 59-86oF (15-30oC).

Manufactured for:

Midwest Veterinary Supply

Lakeville, MN 55044

Midwestvetsupply.com

MADE IN USA